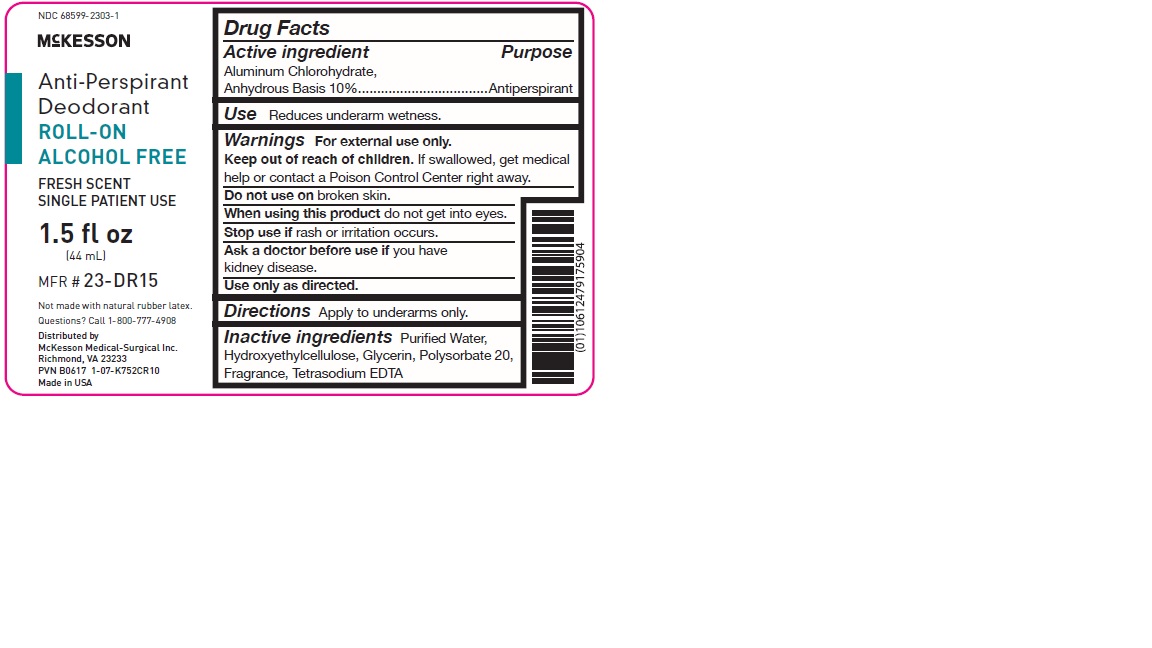 DRUG LABEL: Roll On Anti-Perspirant (Alcohol Free)
NDC: 68599-2303 | Form: SOLUTION
Manufacturer: McKesson Medical-Surgical, Inc.
Category: otc | Type: HUMAN OTC DRUG LABEL
Date: 20241115

ACTIVE INGREDIENTS: ALUMINUM CHLOROHYDRATE 0.1 mg/1 mL
INACTIVE INGREDIENTS: WATER; HYDROXYETHYL CELLULOSE (2000 MPA.S AT 1%); GLYCERIN; POLYSORBATE 20; EDETATE SODIUM

Roll On Anti-Perspirant (Alcohol Free)

Drug Facts

Active ingredient

Aluminum Chlorohydrate, Anhydrous Basis 10%

Purpose

Antiperspirant

Use

Reduces underarm wetness.

Warnings

FOR EXTERNAL USE ONLY.

KEEP OUT OF REACH OF CHILDREN.

Do not use on broken skin.

Stop use if rash or irritation occurs.

Ask a doctor before use if you have kidney disease. If swallowed, get medical help or contact a Poison Control Center immediately. Use only as directed.

Directions

Apply to underarms only.

Inactive ingredients

Purified Water, Hydroxyethylcellulose, Glycerin, Polysorbate 20, Fragrance, Tetrasodium EDTA

PRINCIPAL DISPLAY PANEL

McKESSON

Medi-Pak™

Anti-Perspirant
Deodorant
Roll-On

• Fresh Scent
• Protects Against

Odor and

Wetness

Alcohol Free

1.5 fl. oz. (44 ml)